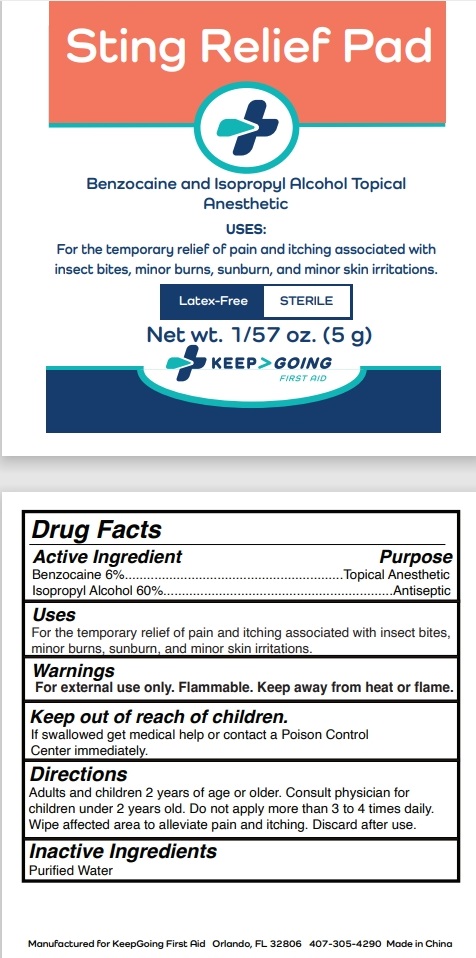 DRUG LABEL: Keep Going  Sting Relief  Pad
NDC: 71734-340 | Form: CLOTH
Manufacturer: JIANGMEN SHUIZIRUN SANITARY ARTICLES CO., LTD.
Category: otc | Type: HUMAN OTC DRUG LABEL
Date: 20240808

ACTIVE INGREDIENTS: BENZOCAINE 6 g/100 g; ISOPROPYL ALCOHOL 60 g/100 g
INACTIVE INGREDIENTS: WATER

DRUG FACTS

Active Ingredient

Benzocaine ..........................6%

Isopropyl Alcohol ................60%

Purpose

Topical Anesthetic And Antiseptic

Uses:

Stops itching and pain associated with insect bites or stings.

Warnings

For external use only.

Flammable .Keep away from fire or flame.

Do not use in the eyes. If irritation or redness occurs, stop use.

Direct contact with open wound will cause stinging.

Keep out of reach of children.

If swallowed get medical help or contact a Posion Control Center immediately.

Directions

Adults and children 2 years of age or older . Cnsult physician for chldren under 2 years old.

Do not apply more than 3 or 4 times daily.

Wipe affected area to alleviate pain and itching.

Discard after use.

Inactive Ingredients:

Purified Water.